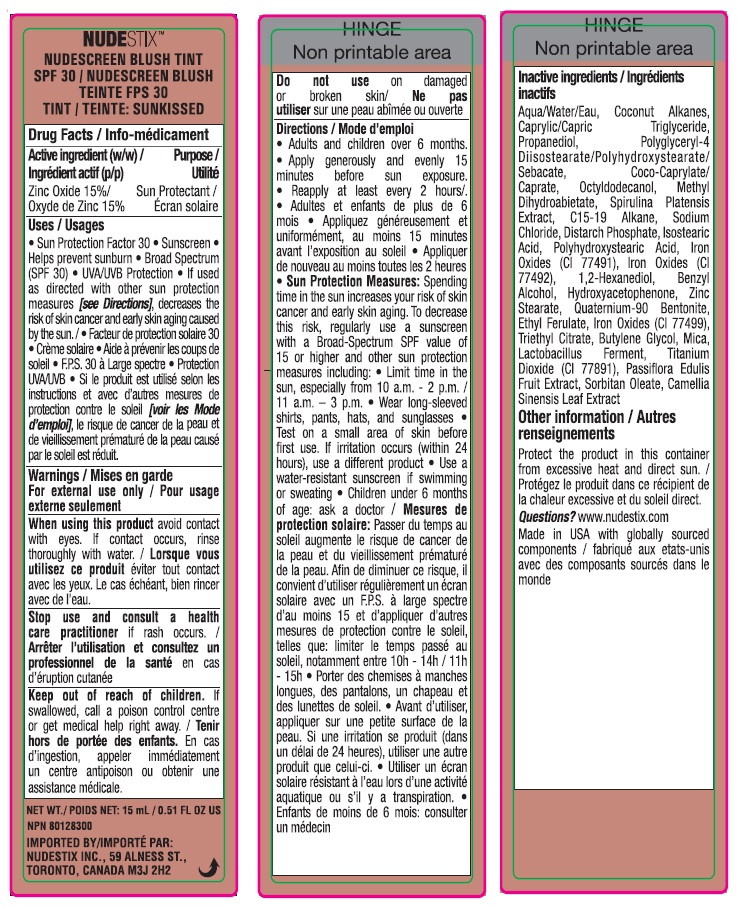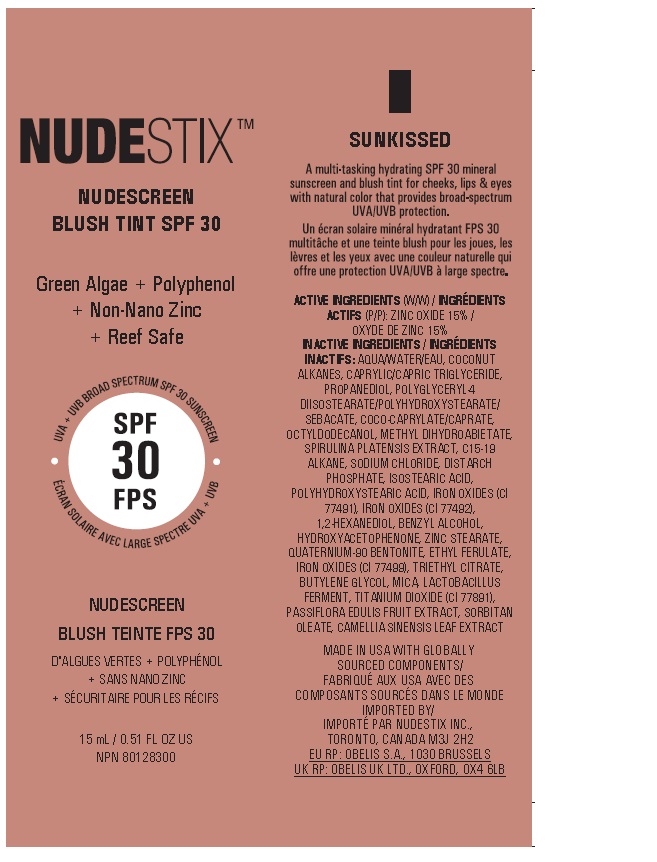 DRUG LABEL: NUDESCREEN BLUSH TINT SPF 30 - SUNKISSED
NDC: 54111-177 | Form: LOTION
Manufacturer: Bentley Laboratories, LLC
Category: otc | Type: HUMAN OTC DRUG LABEL
Date: 20250109

ACTIVE INGREDIENTS: ZINC OXIDE 15 g/100 mL
INACTIVE INGREDIENTS: WATER; COCONUT ALKANES; MEDIUM-CHAIN TRIGLYCERIDES; PROPANEDIOL; POLYGLYCERYL-4 DIISOSTEARATE/POLYHYDROXYSTEARATE/SEBACATE; COCO-CAPRYLATE/CAPRATE; OCTYLDODECANOL; METHYL DIHYDROABIETATE; ARTHROSPIRA PLATENSIS; C15-19 ALKANE; SODIUM CHLORIDE; DISTARCH PHOSPHATE, CORN; ISOSTEARIC ACID; POLYHYDROXYSTEARIC ACID (2300 MW); FERRIC OXIDE RED; FERRIC OXIDE YELLOW; 1,2-HEXANEDIOL; BENZYL ALCOHOL; HYDROXYACETOPHENONE; ZINC STEARATE; QUATERNIUM-90 BENTONITE; ETHYL FERULATE; FERROSOFERRIC OXIDE; TRIETHYL CITRATE; BUTYLENE GLYCOL; MICA; LIMOSILACTOBACILLUS FERMENTUM; TITANIUM DIOXIDE; PASSIFLORA EDULIS FRUIT; SORBITAN MONOOLEATE; GREEN TEA LEAF

NUDESTIX™ NUDESCREEN BLUSH TINT SPF 30 - SUNKISSED

ACTIVE INGREDIENT

Drug Facts / Info-Médicament

ACTIVE INGREDIENTS (W/W) / INGRÉDIENTS
ACTIFS (P/P): ZINC OXIDE 15% /
OXYDE DE ZINC 15%

Purpose / Utilite

Sun Protectant

INDICATIONS AND USAGE

Uses / Usages • Sun Protection Factor
30 • Sunscreen • Helps prevent sunburn
• Broad Spectrum (SPF 30) • UVA/UVB
Protection • If used as directed with other
sun protection measures [see Directions],
decreases the risk of skin cancer and early
skin aging caused by the sun. / • Facteur de
protection solaire 30 • Crème solaire • Aide
à prévenir les coups de soleil • F.P.S. 30 à
Large spectre • Protection UVA/UVB • Si le
produit est utilisé selon les instructions et avec
d’autres mesures de protection contre le soleil
[voir les Mode d’emploi], le risque de cancer
de la peau et de vieillissement prématuré de la
peau causé par le soleil est réduit.

Warnings / Mises en garde

For external use only / Pour usage
externe seulement

When using this product avoid contact
with eyes. If contact occurs, rinse
thoroughly with water. / Lorsque vous
utilisez ce produit éviter tout contact
avec les yeux. Le cas échéant, bien rincer
avec de l’eau.

Stop use and consult a health
care practitioner if rash occurs. /
Arrêter l’utilisation et consultez un
professionnel de la santé en cas
d’éruption cutanée

Keep out of reach of children. If
swallowed, call a poison control centre
or get medical help right away. / Tenir
hors de portée des enfants. En cas
d’ingestion, appeler immédiatement
un centre antipoison ou obtenir une
assistance médicale.

Do not use on damaged
or broken skin/ Ne pas
utiliser sur une peau abîmée ou ouverte

DOSAGE AND ADMINISTRATION

Directions / Mode d’emploi
• Adults and children over 6 months.
• Apply generously and evenly
15 minutes before sun exposure.
• Reapply at least every 2 hours/.
• Adultes et enfants de plus de 6 mois
• Appliquer abondamment/généreusement
(et uniformément) 15 minutes avant
l’exposition au soleil • Appliquer de
nouveau au moins toutes les 2 heures
• Sun Protection Measures: Spending
time in the sun increases your risk of skin
cancer and early skin aging. To decrease
this risk, regularly use a sunscreen
with a Broad-Spectrum SPF value of
15 or higher and other sun protection
measures including: • limit time in the
sun, especially from 10 a.m. - 2 p.m. /
11 a.m. – 3 p.m. • Wear long-sleeved
shirts, pants, hats, and sunglasses
• Test on a small area of skin before first use.
If irritation occurs (within 24 hours), use a different
product • Use a water-resistant sunscreen if
swimming or sweating • Children under 6 months
of age: ask a doctor / Mesures de protection
solaire: Passer du temps au soleil augmente le
risque de cancer de la peau et du vieillissement
prématuré de la peau. Afin de diminuer ce risque,
il convient d’utiliser régulièrement un écran solaire
avec un F.P.S. à large spectre d’au moins 15 et
d’appliquer d’autres mesures de protection contre
le soleil, telles que: limiter le temps passé au soleil,
notamment entre 10h - 14h / 11h - 15h • Porter
des chemises à manches longues, des pantalons,
un chapeau et des lunettes de soleil. • Avant
d’utiliser, appliquer sur une petite surface de la peau.
Si une irritation se produit (dans un délai de
24 heures), utiliser une autre produit que celui-ci.
• Utiliser un écran solaire résistant à l’eau lors
d’une activité aquatique ou s’il y a transpiration.
• Enfants de moins de 6 mois: consulter un médecin

INACTIVE INGREDIENTS / INGRÉDIENTS
INACTIFS:AQUA/WATER/EAU, COCONUT
ALKANES, CAPRYLIC/CAPRIC TRIGLYCERIDE,
PROPANEDIOL, POLYGLYCERYL-4
DIISOSTEARATE/POLYHYDROXYSTEARATE/
SEBACATE, COCO-CAPRYLATE/CAPRATE,
OCTYLDODECANOL, METHYL DIHYDROABIETATE,
SPIRULINA PLATENSIS EXTRACT, C15-19
ALKANE, SODIUM CHLORIDE, DISTARCH
PHOSPHATE, ISOSTEARIC ACID,
POLYHYDROXYSTEARIC ACID, IRON OXIDES (CI
77491), IRON OXIDES (CI 77492),
1,2-HEXANEDIOL, BENZYL ALCOHOL,
HYDROXYACETOPHENONE, ZINC STEARATE,
QUATERNIUM-90 BENTONITE, ETHYL FERULATE,
IRON OXIDES (CI 77499), TRIETHYL CITRATE,
BUTYLENE GLYCOL, MICA, LACTOBACILLUS
FERMENT, TITANIUM DIOXIDE (CI 77891),
PASSIFLORA EDULIS FRUIT EXTRACT, SORBITAN
OLEATE, CAMELLIA SINENSIS
LEAF EXTRACT

Other information/ Autres renseignements
Protect the product in this container from excessive
heat and direct sun.
/ Protégez le produit dans ce récipient de la chaleur
excessive et du soleil direct.

Questions? www.nudestix.com
Made in USA with globally sourced components
/ fabriqué aux etats-unis avec des composants
sourcés dans le monde

NUDESTIX™ NUDESCREEN BLUSH TINT SPF 30 - SUNKISSED

NUDESTIX TM

NUDESCREEN

BLUSH TlNT SPF 30

SUNKISSED

15 ML / 0.51 FL OZ US

MADE IN USA WITH GLOBALLY
SOURCED COMPONENTS/
FABRIQUÉ AUX USA AVEC DES
COMPOSANTS SOURCÉS DANS LE MONDE
IMPORTED BY/
IMPORTÉ PAR NUDESTIX INC.,
TORONTO, CANADA M3J 2H2
EU RP: OBELIS S.A., 1030 BRUSSELS
UK RP: OBELIS UK LTD., OXFORD, OX4 6LB

Tube

Carton

res